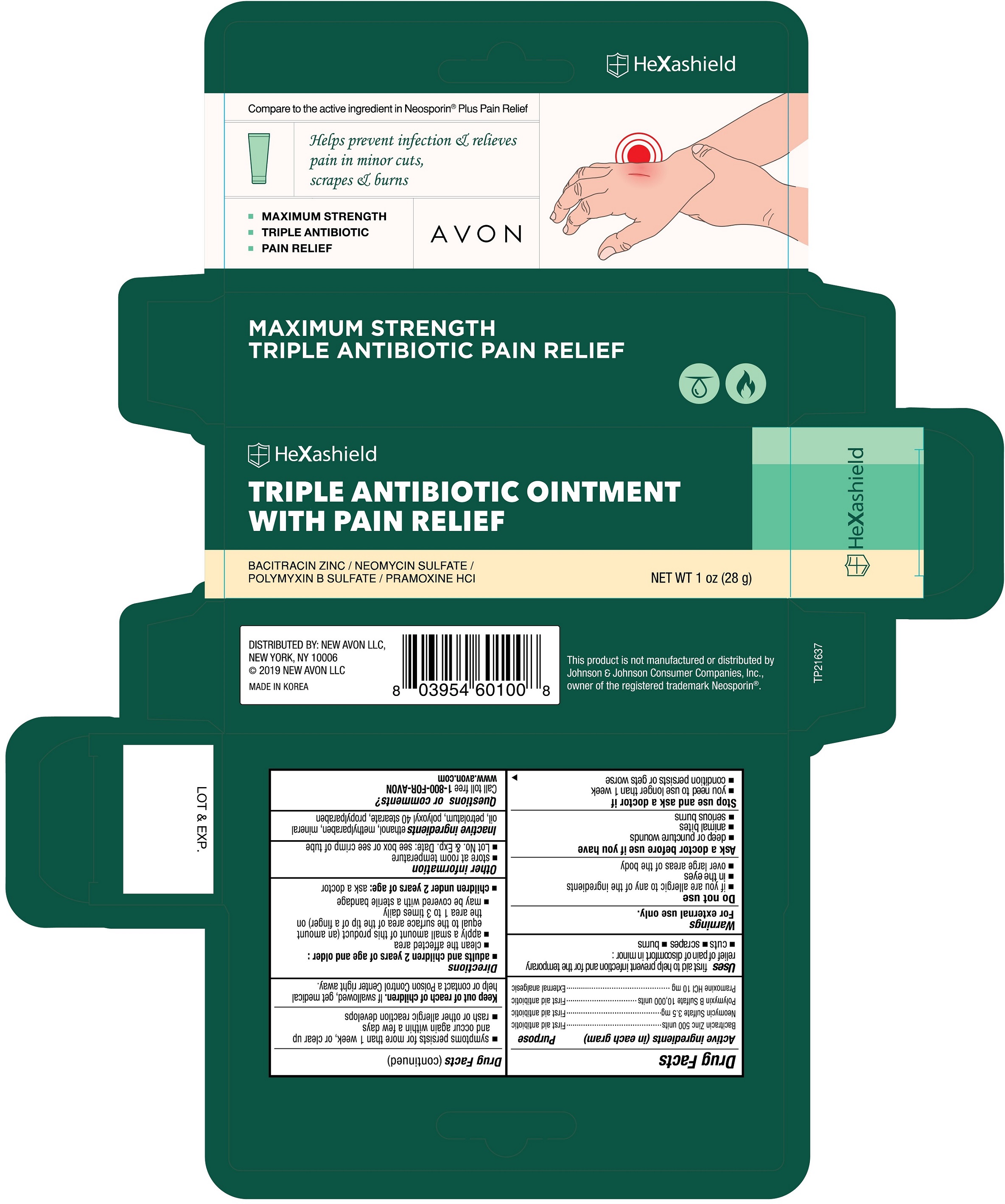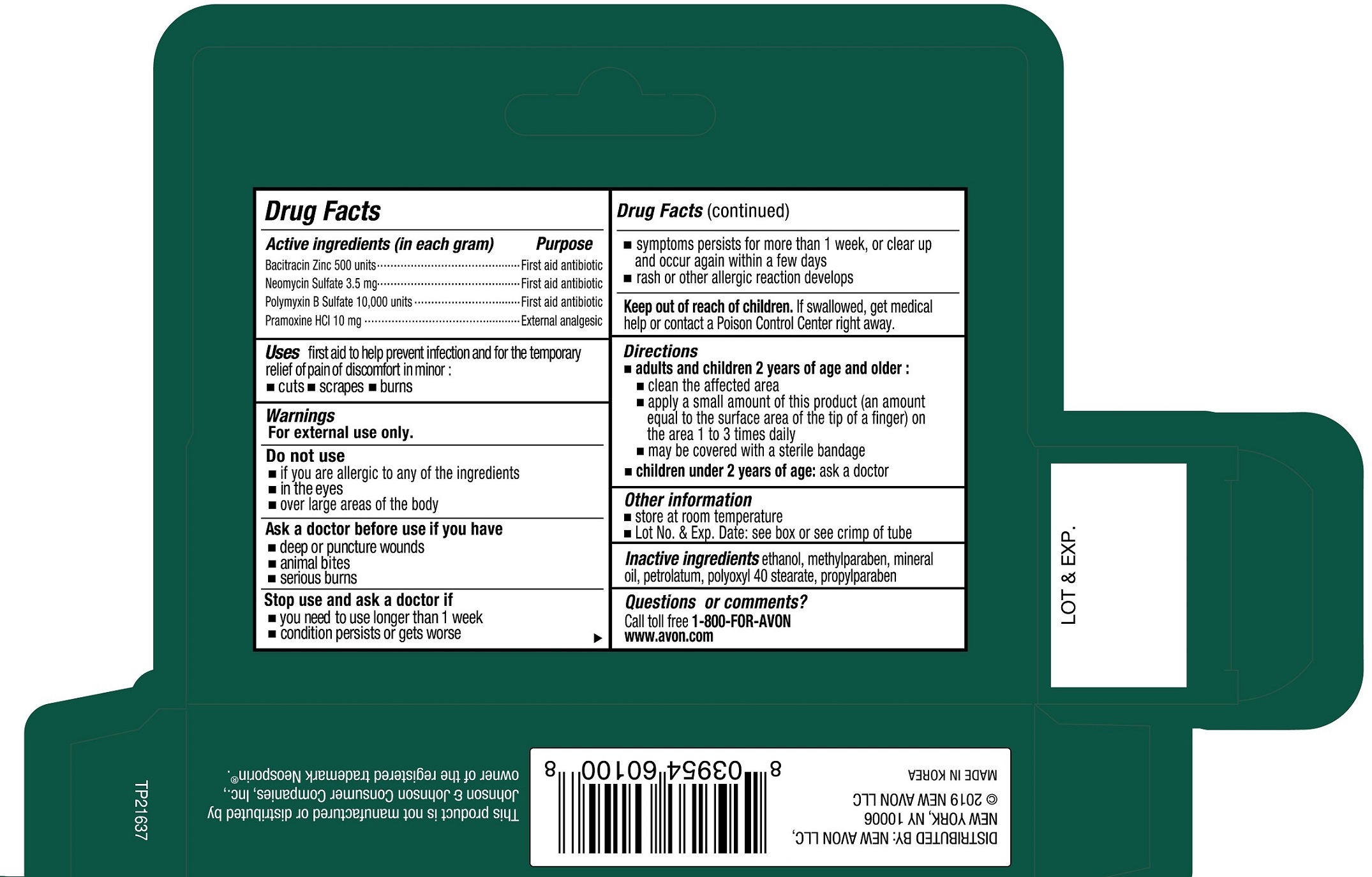 DRUG LABEL: AVON HeXashield Triple Antibiotic with Pain Relief
NDC: 43136-100 | Form: OINTMENT
Manufacturer: Tai Guk Pharm. Co., Ltd.
Category: otc | Type: HUMAN OTC DRUG LABEL
Date: 20250101

ACTIVE INGREDIENTS: POLYMYXIN B SULFATE 10000 [USP'U]/1 g; NEOMYCIN SULFATE 3.5 mg/1 g; BACITRACIN ZINC 500 [USP'U]/1 g; PRAMOXINE HYDROCHLORIDE 10 mg/1 g
INACTIVE INGREDIENTS: PETROLATUM

AVON HeXashield Triple Antibiotic Ointment with Pain Relief

Active Ingredients(in each gram)

Bacitracin Zinc 500 units

Neomycin Sulfate 3.5 mg

Polymyxin B Sulfate 10,000 units

Pramoxine HCl 10 mg

Purpose

First aid antibiotic

External analgesic

Uses

first aid to help prevent infection and for temporary relief of pain or discomfort in minor:

- cuts
- scrapes
- burns

Warnings

For external use only.

Do not use

- if you are allergic to any of the ingredients
- in the eyes
- over large areas of the body

Ask a doctor before use if you have

- deep or puncture wounds
- animal bites
- serious burns

Stop use and ask a doctor if

- you need to use longer than 1 week
- condition persists or gets worse
- symptoms persist for more than 1 week, or clear up and occur again within a few days
- rash or other allergic reaction develops

Keep out of reach of children.

If swallowed, get medical help or contact a Poison Control Center right away.

Directions

- adults and children 2 years of age or older:
- clean the affected area
- apply a small amount of this product (an amount equal to the surface area of the tip of a finger) on the area 1 to 3 times daily
- may be covered with a sterile bandage
- children under 2 years of age: ask a doctor

Other information

- store at room temperature
- Lot No. & Exp. Date: see box or see crimp of tube

Inactive Ingredients

ethanol, methylparaben, mineral oil, petrolatum, polyoxyl 40 stearate, propylparaben

Questions or comments?

Call toll free 1-800-FOR-AVON

www.avon.com

Principal Display Panel

Compare to the active ingredient in Neosporin®Plus Pain Relief

Helps prevent infection & relieves pain in minor cuts, scrapes & burns

- MAXIMUM STRENGTH
- TRIPLE ANTIBIOTIC
- PAIN RELIEF

AVON

HeXashield

TRIPLE ANTIBIOTIC OINTMENT WITH PAIN RELIEF

BACITRACIN ZINC / NEOMYCIN SULFATE / POLYMYXIN B SULFATE / PRAMOXINE HCl

NET WT 1 oz (28g)